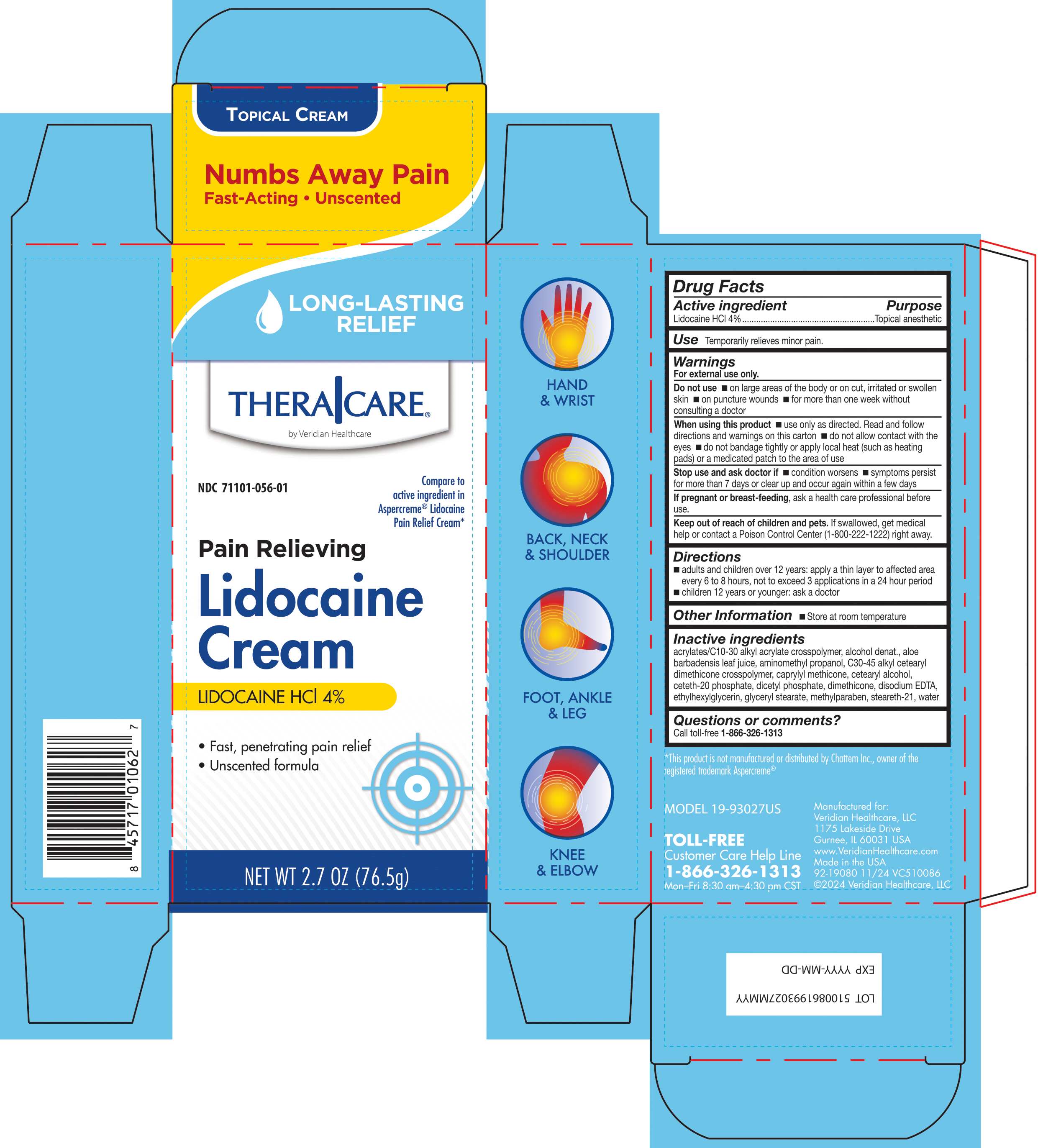 DRUG LABEL: TheraCare Pain Relieving Lidocaine Cream
NDC: 71101-056 | Form: CREAM
Manufacturer: Veridian Healthcare	
Category: otc | Type: HUMAN OTC DRUG LABEL
Date: 20250203

ACTIVE INGREDIENTS: LIDOCAINE HYDROCHLORIDE 4 g/100 g
INACTIVE INGREDIENTS: WATER; ALCOHOL; ACRYLATES/C10-30 ALKYL ACRYLATE CROSSPOLYMER (60000 MPA.S); AMINOMETHYLPROPANOL; DIMETHICONE; EDETATE DISODIUM ANHYDROUS; GLYCERYL STEARATE; C30-45 ALKYL CETEARYL DIMETHICONE CROSSPOLYMER; ALOE VERA LEAF; CAPRYLYL TRISILOXANE; CETETH-20 PHOSPHATE; STEARETH-21; CETOSTEARYL ALCOHOL; DICETYL PHOSPHATE; ETHYLHEXYLGLYCERIN; METHYLPARABEN

TheraCare Pain Relieving Lidocaine Cream

Active ingredient

Lidocaine HCl 4%

Purpose

Topical anesthetic

Use

temporarily relieves minor pain

Warnings

For external use only. Avoid contact with eyes.

Do not use

- on large areas of the body or on cut, irritated or swollen skin
- on puncture wounds
- for more than one week without consulting a doctor

When using this product

- use only as directed. Read and follow all directions and warnings on this carton.
- do not allow contact with the eyes and mucus membranes
- do not bandage or apply local heat (such as heating pads) to the area of use

Stop use and ask a doctor if

- condition worsens
- symptoms persist for more than 7 days or clear up and occur again within a few days

If pregnant or breast-feeding,

ask a health professional before use.

Keep out of reach of children.

If swallowed, get medical help or contact a Poison Control Center (800-222-1222) right away.

Directions

adults and children over 12 years:

- apply a thin layer to affected area every 6 to 8 hours, not to exceed 3 applications in a 24 hour period

children 12 years or younger: ask a doctor

Inactive ingredients

acrylates/C10-30 alkyl acrylate crosspolymer, alcohol denat., aloe barbadensis leaf juice, aminomethyl propanol, C30-45 alkyl cetearyl dimethicone crosspolymer, caprylylmethicone, cetearyl alcohol, ceteth-20phosphate, dicetyl phosphate, dimethicone, disodium EDTA, ethylhexylglycerin, glyceryl stearate, methylparaben, steareth-21, water